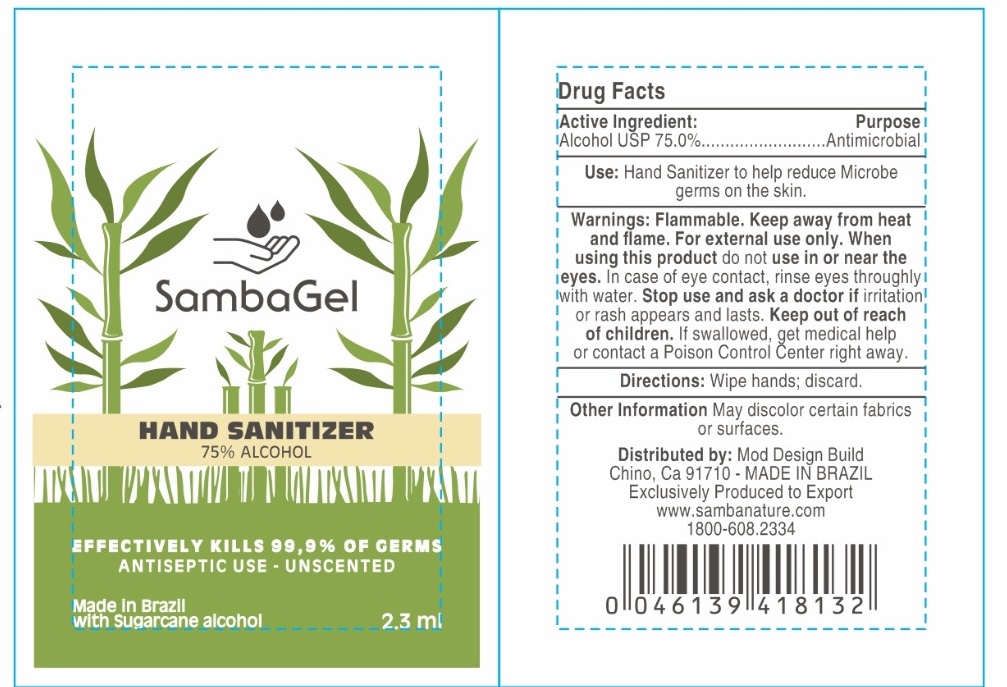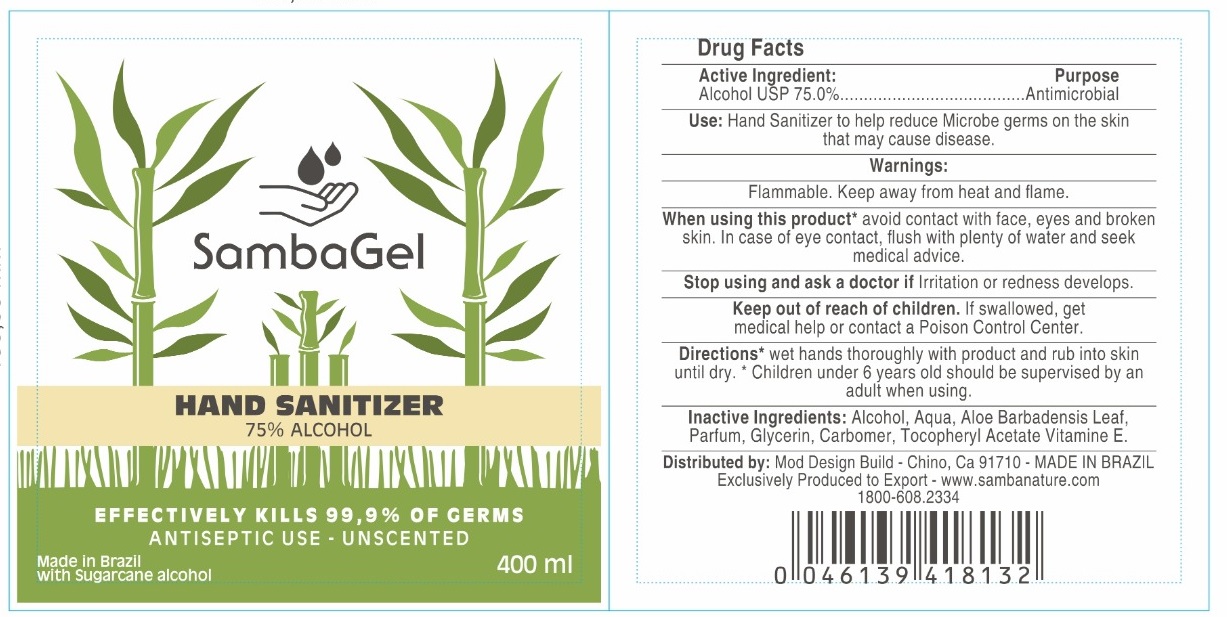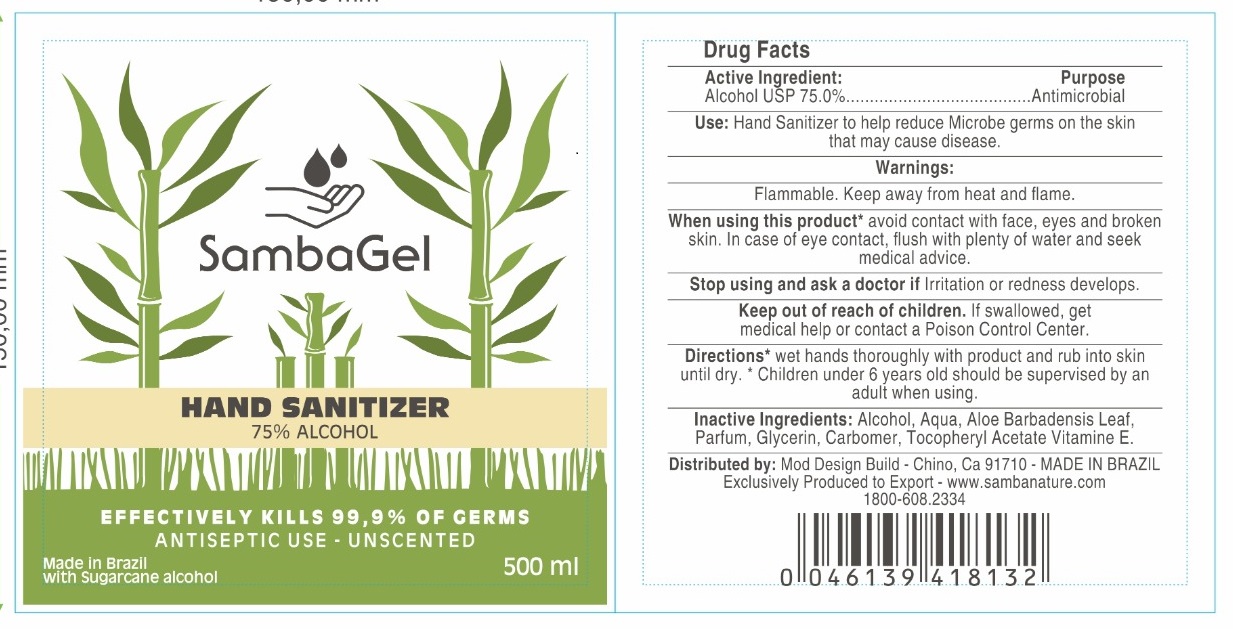 DRUG LABEL: SambaGel
NDC: 80214-001 | Form: GEL
Manufacturer: MOD DESIGN BUILD
Category: otc | Type: HUMAN OTC DRUG LABEL
Date: 20201207

ACTIVE INGREDIENTS: ALCOHOL 75 mL/100 mL
INACTIVE INGREDIENTS: WATER; CARBOMER HOMOPOLYMER, UNSPECIFIED TYPE; GLYCERIN; .ALPHA.-TOCOPHEROL ACETATE; ALOE VERA LEAF

Active Ingredient

Alcohol USP 75.0%

Purpose

Antimicrobial

Use

Hand Sanitizer to help reduce bacteria on the skin that may cause disease.

Warnings

Flammable. Keep away from heat and flame

When using this product avoid contact with face, eyes and broken skin. In case of eye contact, flush with plenty of water and seek medical advice.

Stop using and ask a doctor if irritation or redness develops.

Keep out of reach of children. If swallowed, get medical help or contact a Poison Control Center.

Directions

- Wet hands thoroughly with product and rub into skin until dry.
- Children under 6 years should be supervised by an adult when using.

Inactive ingredients

Alcohol, Aqua, Aloe Barbadensis Leaf, Parfum, Glycerin, Carbomer, Tocopheryl Acetate, Vitamin E